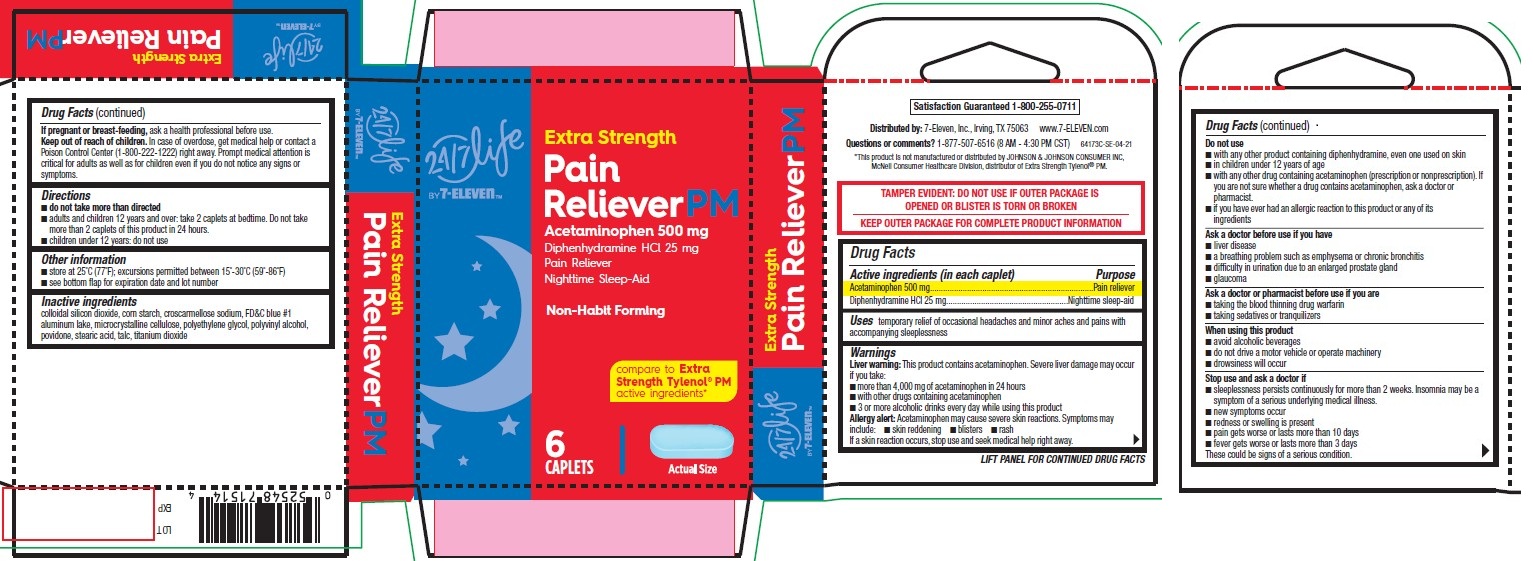 DRUG LABEL: Pain Reliever PM, Extra Strength, 24-7 Life by 7-Eleven
NDC: 66715-8158 | Form: TABLET, FILM COATED
Manufacturer: Lil' Drug Store Products, Inc.
Category: otc | Type: HUMAN OTC DRUG LABEL
Date: 20251212

ACTIVE INGREDIENTS: DIPHENHYDRAMINE HYDROCHLORIDE 25 mg/1 1; ACETAMINOPHEN 500 mg/1 1
INACTIVE INGREDIENTS: SILICON DIOXIDE; TALC; MICROCRYSTALLINE CELLULOSE; POLYETHYLENE GLYCOL, UNSPECIFIED; POVIDONE, UNSPECIFIED; STARCH, CORN; CROSCARMELLOSE SODIUM; FD&C BLUE NO. 1 ALUMINUM LAKE; STEARIC ACID; TITANIUM DIOXIDE; POLYVINYL ALCOHOL, UNSPECIFIED

Pain Reliever PM, Extra Strength, 24/7 Life by 7-ElevenTM

Drug Facts

Active ingredients

Active ingredients (in each caplet)

Acetaminophen 500 mg

Diphenhydramine HCl 25 mg

Purpose

Pain reliever

Nighttime sleep-aid

Uses

temporary relief of occasional headaches and minor aches and pains with accompanying sleeplessness

Warnings

Liver warning

Liver warning: This product contains acetaminophen. Severe liver damage may occur if you take:

- more than 4,000 mg of acetaminophen in 24 hours
- with other drugs containing acetaminophen
- 3 or more alcoholic drinks every day while using this product

Allergy alert

Allergy alert: Acetaminophen may cause severe skin reactions. Symptoms may include:

- skin reddening
- blisters
- rash

If a skin reaction occurs, stop use and seek medical help right away.

Do not use

- with any other product containing diphenhydramine, even one used on skin
- in children under 12 years of age
- with any other drug containing acetaminophen (prescription or nonprescription). If you are not sure whether a drug contains acetaminophen, ask a doctor or pharmacist.
- if you have ever had an allergic reaction to this product or any of its ingredients

Ask a doctor before use if you have

- liver disease
- a breathing problem such as emphysema or chronic bronchitis
- difficulty in urination due to an enlarged prostate gland
- glaucoma

Ask a doctor or pharmacist before use if you are

- taking the blood thinning drug warfarin
- taking sedatives or tranquilizers

When using this product

- avoid alcoholic beverages
- do not drive a motor vehicle or operate machinery
- drowsiness will occur

Stop use and ask a doctor if

- sleeplessness persists continuously for more than 2 weeks. Insomnia may be a symptom of a serious underlying medical illness.
- new symptoms occur
- redness or swelling is present
- pain gets worse or lasts more than 10 days
- fever gets worse or lasts more than 3 days

These could be signs of a serious condition.

If pregnant or breast-feeding, ask a health professional before use.

Keep out of reach of children. In case of overdose, get medical help or contact a Poison Control Center (1-800-222-1222) right away. Prompt medical attention is critical for adults as well as for children even if you do not notice any signs or symptoms.

Directions

- do not take more than directed
- adults and children 12 years and over: take 2 caplets at bedtime. Do not take more than 2 caplets of this product in 24 hours.
- children under 12 years: do not use

Other information

- store at 25°C (77°F); excursions permitted between 15°-30°C (59°-86°F)
- see bottom flap for expiration date and lot number

Inactive ingredients

colloidal silicon dioxide, corn starch, croscarmellose sodium, FD&C blue #1 aluminum lake, microcrystalline cellulose, polyethylene glycol, polyvinyl alcohol, povidone, stearic acid, talc, titanium dioxide

Pain reliever PM, Extra Strength, 24/7 Life b 7-ElevenTM

[ 24/7 Life by 7-ElevenTM logo]

Pain Reliever PM, Extra Strength, 24/7 Life by 7-ElevenTM - PDP/Package

[ 24/7 Life by 7-ElevenTM logo]

Extra Strength

Pain

RelieverPM

Acetaminophen 500 mg

Diphenhydramine HCl 25 mg

Pain Reliever

Nighttime Sleep-Aid

Non-Habit Forming

compare to Extra

Strength Tylenol® PM

active ingredients*

6

CAPLETS

[caplet image]

Actual Size